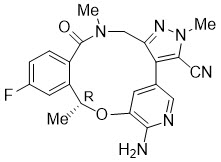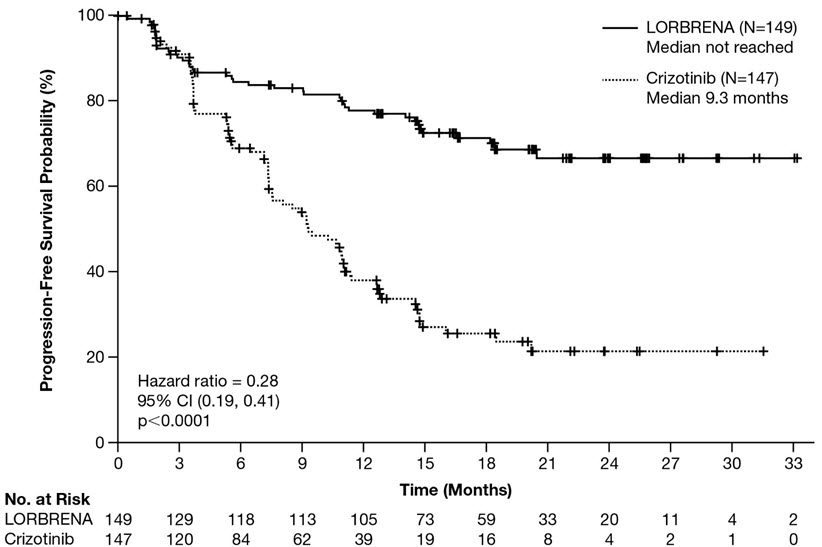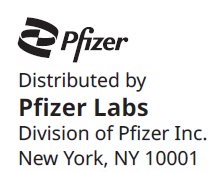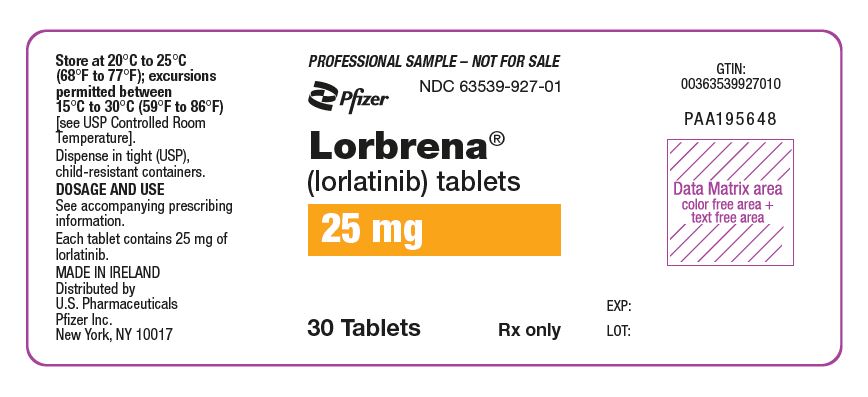 DRUG LABEL: Lorbrena
NDC: 63539-927 | Form: TABLET, FILM COATED
Manufacturer: U.S. Pharmaceuticals
Category: prescription | Type: HUMAN PRESCRIPTION DRUG LABEL
Date: 20260213

ACTIVE INGREDIENTS: LORLATINIB 25 mg/1 1
INACTIVE INGREDIENTS: MICROCRYSTALLINE CELLULOSE; ANHYDROUS DIBASIC CALCIUM PHOSPHATE; SODIUM STARCH GLYCOLATE TYPE A POTATO; MAGNESIUM STEARATE; HYPROMELLOSE, UNSPECIFIED; LACTOSE MONOHYDRATE; TRIACETIN; POLYETHYLENE GLYCOL, UNSPECIFIED; TITANIUM DIOXIDE; FERROSOFERRIC OXIDE; FERRIC OXIDE RED

HIGHLIGHTS OF PRESCRIBING INFORMATION

These highlights do not include all the information needed to use LORBRENA safely and effectively. See full prescribing information for LORBRENA.
LORBRENA® (lorlatinib) tablets, for oral use
Initial U.S. Approval: 2018

RECENT MAJOR CHANGES

Dosage Modifications for Drug Interactions (2.4) | 1/2026
Recommended Dosage for Severe Hepatic Impairment (2.5) | 1/2026
Recommended Dosage for Renal Impairment (2.6) | 1/2026

1 INDICATIONS AND USAGE

LORBRENA is a kinase inhibitor indicated for the treatment of adult patients with metastatic non-small cell lung cancer (NSCLC) whose tumors are anaplastic lymphoma kinase (ALK)-positive as detected by an FDA-approved test. (1, 2.1)

2 DOSAGE AND ADMINISTRATION

Recommended dosage: 100 mg orally once daily. (2.2)

Severe Hepatic Impairment: 50 mg orally once daily. (2.5, 8.6, 12.3)

Renal Impairment: 75 mg orally once daily. (2.6, 8.7, 12.3)

3 DOSAGE FORMS AND STRENGTHS

Tablets: 25 mg or 100 mg. (3)

4 CONTRAINDICATIONS

Concomitant use with strong CYP3A inducers. (4)

5 WARNINGS AND PRECAUTIONS

- Risk of Serious Hepatotoxicity with Concomitant Use of Strong CYP3A Inducers: Discontinue strong CYP3A inducers for 3 plasma half-lives of the strong CYP3A inducer prior to initiating LORBRENA. (2.4, 5.1)
- Central Nervous System (CNS) Effects: CNS effects include seizures, psychotic effects and changes in cognitive function, mood (including suicidal ideation), speech, mental status, and sleep. Withhold and resume LORBRENA at same or reduced dose or permanently discontinue LORBRENA based on severity. (2.3, 5.2)
- Hyperlipidemia: Initiate or increase the dose of lipid-lowering agents. Withhold and resume LORBRENA at same or reduced dose based on severity. (2.3, 5.3)
- Atrioventricular Block: Withhold and resume LORBRENA at same or reduced dose based on severity. (2.3, 5.4)
- Interstitial Lung Disease/Pneumonitis: Immediately withhold LORBRENA in patients with suspected ILD/pneumonitis. Permanently discontinue LORBRENA for treatment-related ILD/pneumonitis of any severity. (2.3, 5.5)
- Hypertension: Monitor blood pressure after 2 weeks and then at least monthly during treatment. For severe hypertension, withhold LORBRENA, then dose reduce or permanently discontinue. (2.3, 5.6)
- Hyperglycemia: Assess fasting serum glucose prior to starting LORBRENA and regularly during treatment. If not adequately controlled with optimal medical management, withhold LORBRENA, then consider dose reduction or permanently discontinue, based on severity. (2.3, 5.7)
- Embryo-Fetal Toxicity: Can cause fetal harm. Advise females of reproductive potential of the potential risk to a fetus. Advise males and females of reproductive potential to use an effective non-hormonal method of contraception. (5.8, 7.2, 8.1, 8.3)

6 ADVERSE REACTIONS

Most common (incidence ≥20%) adverse reactions and Grade 3–4 laboratory abnormalities are edema, peripheral neuropathy, weight gain, cognitive effects, fatigue, dyspnea, arthralgia, diarrhea, mood effects, hypercholesterolemia, hypertriglyceridemia, and cough. (6.1)

To report SUSPECTED ADVERSE REACTIONS, contact Pfizer Inc. at 1-800-438-1985 or www.pfizer.com or FDA at 1-800-FDA-1088 or www.fda.gov/medwatch.

7 DRUG INTERACTIONS

- Strong CYP3A Inducers: Contraindicated. (2.4, 7.1)
- Moderate CYP3A Inducers: Avoid concomitant use. If concomitant use cannot be avoided, increase the LORBRENA dose. (2.4, 7.1)
- Strong CYP3A Inhibitors: Avoid concomitant use; reduce LORBRENA dose if concomitant use cannot be avoided. (2.4, 7.1)
- Fluconazole: Avoid concomitant use; reduce LORBRENA dose if concomitant use cannot be avoided. (2.4, 7.1)
- Certain CYP3A Substrates: Avoid concomitant use with CYP3A substrates for which minimal concentration changes may lead to serious therapeutic failures. (7.2)
- Certain P-gp Substrates: Avoid concomitant use with P-gp substrates for which minimal concentration changes may lead to serious therapeutic failures. (7.2)

8 USE IN SPECIFIC POPULATIONS

Lactation: Advise not to breastfeed. (8.2)

FULL PRESCRIBING INFORMATION

1 INDICATIONS AND USAGE

LORBRENA® is indicated for the treatment of adult patients with metastatic non-small cell lung cancer (NSCLC) whose tumors are anaplastic lymphoma kinase (ALK)-positive as detected by an FDA-approved test.

2 DOSAGE AND ADMINISTRATION

2.1 Patient Selection

Select patients for the treatment of metastatic NSCLC with LORBRENA based on the presence of ALK positivity in tumor specimens [see Indications and Usage (1) and Clinical Studies (14)].

Information on FDA-approved tests for the detection of ALK rearrangements in NSCLC is available at http://www.fda.gov/CompanionDiagnostics.

2.2 Recommended Dosage

The recommended dosage of LORBRENA is 100 mg orally once daily, with or without food, until disease progression or unacceptable toxicity [see Clinical Pharmacology (12.3)].

Swallow tablets whole. Do not chew, crush or split tablets. Do not ingest if tablets are broken, cracked, or otherwise not intact.

Take LORBRENA at the same time each day. If a dose is missed, then take the missed dose unless the next dose is due within 4 hours. Do not take 2 doses at the same time to make up for a missed dose.

Do not take an additional dose if vomiting occurs after LORBRENA but continue with the next scheduled dose.

2.3 Dosage Modifications for Adverse Reactions

The recommended dose reductions are:

- First dose reduction: LORBRENA 75 mg orally once daily
- Second dose reduction: LORBRENA 50 mg orally once daily

Permanently discontinue LORBRENA in patients who are unable to tolerate 50 mg orally once daily.

Dosage modifications for adverse reactions of LORBRENA are provided in Table 1.

Table 1 Recommended LORBRENA Dosage Modifications for Adverse Reactions
Adverse Reaction [Grade based on National Cancer Institute (NCI) Common Terminology Criteria for Adverse Events (CTCAE) version 4.03.] | Dosage Modifications
Central Nervous System Effects [see Warnings and Precautions (5.2)]
Grade 1 | Continue at the same dose or withhold the dose until recovery to baseline. Resume LORBRENA at the same dose or at a reduced dose.
Grade 2 OR Grade 3 | Withhold dose until Grade 0 or 1. Resume LORBRENA at a reduced dose.
Grade 4 | Permanently discontinue LORBRENA.
Hyperlipidemia [see Warnings and Precautions (5.3)]
Grade 4 hypercholesterolemia OR Grade 4 hypertriglyceridemia | Withhold LORBRENA until recovery of hypercholesterolemia and/or hypertriglyceridemia to less than or equal to Grade 2. Resume LORBRENA at the same dose. If severe hypercholesterolemia and/or hypertriglyceridemia recurs, resume LORBRENA at a reduced dose.
Atrioventricular (AV) Block [see Warnings and Precautions (5.4)]
Second-degree AV block | Withhold LORBRENA until PR interval is less than 200 ms. Resume LORBRENA at a reduced dose.
First occurrence of complete AV block | Withhold LORBRENA until; - pacemaker placed OR - PR interval less than 200 ms.; If a pacemaker is placed, resume LORBRENA at the same dose. If no pacemaker is placed, resume LORBRENA at a reduced dose.
Recurrent complete AV block | Place pacemaker or permanently discontinue LORBRENA.
Interstitial Lung Disease (ILD)/Pneumonitis [see Warnings and Precautions (5.5)]
Any Grade treatment–related ILD/Pneumonitis | Permanently discontinue LORBRENA.
Hypertension [see Warnings and Precautions (5.6)]
Grade 3 (SBP greater than or equal to 160 mmHg or DBP greater than or equal to 100 mmHg; medical intervention indicated; more than one antihypertensive drug, or more intensive therapy than previously used indicated) | Withhold LORBRENA until hypertension has recovered to Grade 1 or less (SBP less than 140 mmHg and DBP less than 90 mmHg), then resume LORBRENA at the same dose. If Grade 3 hypertension recurs, withhold LORBRENA until recovery to Grade 1 or less, and resume at a reduced dose. If adequate hypertension control cannot be achieved with optimal medical management, permanently discontinue LORBRENA.
Grade 4 (life-threatening consequences, urgent intervention indicated) | Withhold LORBRENA until recovery to Grade 1 or less, and resume at a reduced dose or permanently discontinue LORBRENA. If Grade 4 hypertension recurs, permanently discontinue LORBRENA.
Hyperglycemia [see Warnings and Precautions (5.7)]
Grade 3 (greater than 250 mg/dL) despite optimal anti-hyperglycemic therapy OR Grade 4 | Withhold LORBRENA until hyperglycemia is adequately controlled, then resume LORBRENA at the next lower dosage. If adequate hyperglycemic control cannot be achieved with optimal medical management, permanently discontinue LORBRENA.
Other Adverse Reactions
Grade 1 OR Grade 2 | Continue LORBRENA at same dose or reduced dose.
Grade 3 OR Grade 4 | Withhold LORBRENA until symptoms resolve to less than or equal to Grade 2 or baseline. Resume LORBRENA at reduced dose.
Abbreviation: AV=atrioventricular; DBP=diastolic blood pressure; SBP=systolic blood pressure.

2.4 Dosage Modifications for Drug Interactions

Strong CYP3A Inducers

LORBRENA is contraindicated in patients taking strong CYP3A inducers. Discontinue strong CYP3A inducers for 3 plasma half-lives of the strong CYP3A inducer prior to initiating LORBRENA [see Contraindications (4), Warnings and Precautions (5.1), Drug Interactions (7.1), Clinical Pharmacology (12.3)].

Moderate CYP3A Inducers

Avoid concomitant use of moderate CYP3A inducers with LORBRENA. If concomitant use with moderate CYP3A inducers is unavoidable, increase the LORBRENA dose to 125 mg once daily [see Drug Interactions (7.1), Clinical Pharmacology (12.3)].

Strong CYP3A Inhibitors

Avoid concomitant use of LORBRENA with strong CYP3A inhibitors. If concomitant use with a strong CYP3A inhibitor is unavoidable, reduce the starting dose of LORBRENA from 100 mg orally once daily to 75 mg orally once daily.

In patients who have had a dose reduction to 75 mg orally once daily due to adverse reactions and who initiate a strong CYP3A inhibitor, reduce the LORBRENA dose to 50 mg orally once daily.

If concomitant use of a strong CYP3A inhibitor is discontinued, increase the LORBRENA dose (after 3 plasma half-lives of the strong CYP3A inhibitor) to the dose that was used before starting the strong inhibitor [see Drug Interactions (7.1), Clinical Pharmacology (12.3)].

Fluconazole

Avoid concomitant use of LORBRENA with fluconazole [see Clinical Pharmacology (12.3)]. If concomitant use is unavoidable, reduce the starting dose of LORBRENA from 100 mg orally once daily to 75 mg orally once daily [see Drug Interactions (7.1), Clinical Pharmacology (12.3)].

2.5 Recommended Dosage for Severe Hepatic Impairment

The recommended dosage of LORBRENA for patients with severe hepatic impairment (Child-Pugh C) is 50 mg orally once daily [see Use in Specific Populations (8.6), Clinical Pharmacology (12.3)].

2.6 Recommended Dosage for Renal Impairment

The recommended dosage of LORBRENA for patients with creatinine clearance [CLcr] 15 to < 30 mL/min (estimated by Cockcroft‑Gault) is 75 mg orally once daily [see Use in Specific Populations (8.7) and Clinical Pharmacology (12.3)].

3 DOSAGE FORMS AND STRENGTHS

Tablets:

- 25 mg: 8 mm round, tan, immediate release, film-coated, debossed with "Pfizer" on one side and "25" and "LLN" on the other side
- 100 mg: 8.5 mm × 17 mm oval, lavender, immediate release, film-coated, debossed with "Pfizer" on one side and "LLN 100" on the other side

4 CONTRAINDICATIONS

LORBRENA is contraindicated in patients taking strong CYP3A inducers, due to the potential for serious hepatotoxicity [see Warnings and Precautions (5.1)].

5 WARNINGS AND PRECAUTIONS

5.1 Risk of Serious Hepatotoxicity with Concomitant Use of Strong CYP3A Inducers

Severe hepatotoxicity occurred in 10 of 12 healthy subjects receiving a single dose of LORBRENA with multiple daily doses of rifampin, a strong CYP3A inducer. Grade 4 alanine aminotransferase (ALT) or aspartate aminotransferase (AST) elevations occurred in 50% of subjects, Grade 3 ALT or AST elevations occurred in 33% and Grade 2 ALT or AST elevations occurred in 8%. ALT or AST elevations occurred within 3 days and returned to within normal limits after a median of 15 days (7 to 34 days); the median time to recovery was 18 days in subjects with Grade 3 or 4 ALT or AST elevations and 7 days in subjects with Grade 2 ALT or AST elevations [see Drug Interactions (7.1)].

LORBRENA is contraindicated in patients taking strong CYP3A inducers. Discontinue strong CYP3A inducers for 3 plasma half-lives of the strong CYP3A inducer prior to initiating LORBRENA [see Contraindications (4), Drug Interactions (7.1)].

5.2 Central Nervous System Effects

A broad spectrum of central nervous system (CNS) effects can occur in patients receiving LORBRENA. These include seizures, psychotic effects and changes in cognitive function, mood (including suicidal ideation), speech, mental status, and sleep. Overall, CNS effects occurred in 52% of the 476 patients who received 100 mg LORBRENA once daily in clinical trials [see Adverse Reactions (6.1)]. Cognitive effects occurred in 28% of the 476 patients; 2.9% of these events were severe (Grade 3 or 4). Mood effects occurred in 21% of patients; 1.7% of these events were severe. Speech effects occurred in 11% of patients; 0.6% of these events were severe. Psychotic effects occurred in 7% of patients; 0.6% of these events were severe. Mental status changes occurred in 1.3% of patients; 1.1% of these events were severe. Seizures occurred in 1.9% of patients, sometimes in conjunction with other neurologic findings. Sleep effects occurred in 12% of patients. The median time to first onset of any CNS effect was 1.4 months (1 day to 3.4 years). Overall, 2.1% of patients required permanent discontinuation of LORBRENA for a CNS effect; 10% required temporary discontinuation and 8% required dose reduction.

Withhold and resume at the same dose or at a reduced dose or permanently discontinue LORBRENA based on severity [see Dosage and Administration (2.3)].

5.3 Hyperlipidemia

Increases in serum cholesterol and triglycerides can occur in patients receiving LORBRENA [see Adverse Reactions (6.1)]. Grade 3 or 4 elevations in total cholesterol occurred in 18% and Grade 3 or 4 elevations in triglycerides occurred in 19% of the 476 patients who received 100 mg LORBRENA once daily. The median time to onset was 15 days for both hypercholesterolemia and hypertriglyceridemia. Approximately 4% and 7% of patients required temporary discontinuation and 1% and 3% of patients required dose reduction of LORBRENA for elevations in cholesterol and in triglycerides in Study B7461001 and Study B7461006, respectively. Eighty-three percent of patients required initiation of lipid-lowering medications, with a median time to onset of start of such medications of 17 days.

Initiate or increase the dose of lipid-lowering agents in patients with hyperlipidemia. Monitor serum cholesterol and triglycerides before initiating LORBRENA, 1 and 2 months after initiating LORBRENA, and periodically thereafter. Withhold and resume at the same dose for the first occurrence; resume at the same or a reduced dose of LORBRENA for recurrence based on severity [see Dosage and Administration (2.3)].

5.4 Atrioventricular Block

PR interval prolongation and atrioventricular (AV) block can occur in patients receiving LORBRENA [see Adverse Reactions (6.1), Clinical Pharmacology (12.2)]. In 476 patients who received 100 mg LORBRENA once daily and who had a baseline electrocardiography (ECG), 1.9% experienced AV block and 0.2% experienced Grade 3 AV block and underwent pacemaker placement.

Monitor ECG prior to initiating LORBRENA and periodically thereafter. Withhold and resume at a reduced dose or at the same dose in patients who undergo pacemaker placement. Permanently discontinue for recurrence in patients without a pacemaker [see Dosage and Administration (2.3)].

5.5 Interstitial Lung Disease/Pneumonitis

Severe or life-threatening pulmonary adverse reactions consistent with interstitial lung disease (ILD)/pneumonitis can occur with LORBRENA. ILD/pneumonitis occurred in 1.9% of patients who received 100 mg LORBRENA once daily, including Grade 3 or 4 ILD/pneumonitis in 0.6% of patients. Four patients (0.8%) discontinued LORBRENA for ILD/pneumonitis.

Promptly investigate for ILD/pneumonitis in any patient who presents with worsening of respiratory symptoms indicative of ILD/pneumonitis (e.g., dyspnea, cough, and fever). Immediately withhold LORBRENA in patients with suspected ILD/pneumonitis. Permanently discontinue LORBRENA for treatment-related ILD/pneumonitis of any severity [see Dosage and Administration (2.3)].

5.6 Hypertension

Hypertension can occur in patients receiving LORBRENA [see Adverse Reactions (6.1)]. Hypertension occurred in 13% of patients who received 100 mg LORBRENA once daily, including Grade 3 or 4 in 6% of patients. The median time to onset of hypertension was 6.4 months (1 day to 2.8 years), and 2.3% of patients temporarily discontinued LORBRENA for hypertension.

Control blood pressure prior to initiation of LORBRENA. Monitor blood pressure after 2 weeks and at least monthly thereafter during treatment with LORBRENA. Withhold and resume at a reduced dose or permanently discontinue LORBRENA based on severity [see Dosage and Administration (2.3)].

5.7 Hyperglycemia

Hyperglycemia can occur in patients receiving LORBRENA [see Adverse Reactions (6.1)]. Hyperglycemia occurred in 9% of patients who received 100 mg LORBRENA, including Grade 3 or 4 in 3.2% of patients. The median time to onset of hyperglycemia was 4.8 months (1 day to 2.9 years), and 0.8% of patients temporarily discontinued LORBRENA for hyperglycemia.

Assess fasting serum glucose prior to initiation of LORBRENA and monitor periodically thereafter. Withhold and resume at a reduced dose or permanently discontinue LORBRENA based on severity [see Dosage and Administration (2.3)].

5.8 Embryo-Fetal Toxicity

Based on findings from animal studies and its mechanism of action, LORBRENA can cause fetal harm when administered to a pregnant woman. Administration of lorlatinib to pregnant rats and rabbits by oral gavage during the period of organogenesis resulted in malformations, increased post-implantation loss, and abortion at maternal exposures that were equal to or less than the human exposure at the recommended dose of 100 mg once daily based on area under the curve (AUC).

Advise pregnant women of the potential risk to a fetus. Advise females of reproductive potential to use an effective non-hormonal method of contraception, since LORBRENA can render hormonal contraceptives ineffective, during treatment with LORBRENA and for at least 6 months after the final dose. Advise males with female partners of reproductive potential to use effective contraception during treatment with LORBRENA and for 3 months after the final dose [see Drug Interactions (7.2), Use in Specific Populations (8.1, 8.3), Nonclinical Toxicology (13.1)].

6 ADVERSE REACTIONS

The following adverse reactions are described elsewhere in the labeling:

- Risk of Serious Hepatotoxicity with Concomitant Use of Strong CYP3A Inducers [see Warnings and Precautions (5.1)]
- Central Nervous System Effects [see Warnings and Precautions (5.2)]
- Hyperlipidemia [see Warnings and Precautions (5.3)]
- Atrioventricular Block [see Warnings and Precautions (5.4)]
- Interstitial Lung Disease/Pneumonitis [see Warnings and Precautions (5.5)]
- Hypertension [see Warnings and Precautions (5.6)]
- Hyperglycemia [see Warnings and Precautions (5.7)]

6.1 Clinical Trials Experience

Because clinical trials are conducted under widely varying conditions, adverse reaction rates observed in the clinical trials of a drug cannot be directly compared to rates in the clinical trials of another drug and may not reflect the rates observed in practice.

The pooled safety population described in the Warnings and Precautions section reflects exposure to LORBRENA in 476 patients who received 100 mg LORBRENA once daily in Study B7461001 (N=327) and Study B7461006 (N=149). Among 476 patients who received LORBRENA, 75% were exposed for 6 months or longer and 61% were exposed for greater than 1 year. In this pooled safety population, the most frequent adverse reactions in ≥ 20% of 476 patients who received LORBRENA were edema (56%), peripheral neuropathy (44%), weight gain (31%), cognitive effects (28%), fatigue (27%), dyspnea (27%), arthralgia (24%), diarrhea (23%), mood effects (21%), and cough (21%). The most frequent Grade 3–4 laboratory abnormalities in ≥ 20% of 476 patients who received LORBRENA were hypercholesterolemia (21%) and hypertriglyceridemia (21%).

Previously Untreated ALK-Positive Metastatic NSCLC (CROWN Study)

The safety of LORBRENA was evaluated in 149 patients with ALK-positive NSCLC in a randomized, open-label, active-controlled trial for the treatment of patients with ALK-positive, locally advanced or metastatic, NSCLC who had not received previous systemic treatment for advanced disease [see Clinical Studies (14)]. The median duration of exposure to LORBRENA was 16.7 months (4 days to 34.3 months) and 76% received LORBRENA for at least 12 months.

Serious adverse reactions occurred in 34% of patients treated with LORBRENA; the most frequently reported serious adverse reactions were pneumonia (4.7%), dyspnea (2.7%), respiratory failure (2.7%), cognitive effects (2.0%), and pyrexia (2.0%). Fatal adverse reactions occurred in 3.4% of patients treated with LORBRENA and included pneumonia (0.7%), respiratory failure (0.7%), cardiac failure acute (0.7%), pulmonary embolism (0.7%), and sudden death (0.7%).

Permanent discontinuation of LORBRENA due to adverse reactions occurred in 6.7% of patients. The most frequent adverse reaction that led to permanent discontinuation of LORBRENA was cognitive effects (1.3%). Adverse reactions leading to dose interruptions occurred in 49% of patients treated with LORBRENA. The most frequent adverse reactions that led to dose interruptions of LORBRENA were hypertriglyceridemia (7%), edema (5%), pneumonia (4.7%) cognitive effects (4.0%), mood effects (4.0%), and hypercholesterolemia (3.4%). Adverse reactions leading to dose reductions occurred in 21% of patients treated with LORBRENA. The most frequent adverse reactions that led to dose reductions were edema (5%), hypertriglyceridemia (4.0%), and peripheral neuropathy (3.4%).

Tables 2 and 3 summarize most frequent adverse reactions and laboratory abnormalities, respectively, in patients treated with LORBRENA in Study B7461006.

Table 2 Adverse Reactions (≥10% for all NCI CTCAE Grades or ≥2% for Grades 3–4) in Patients Treated with LORBRENA in Study B7461006 [Adverse reactions were graded using NCI CTCAE version 4.03.]
Adverse Reaction | LORBRENA N=149 |  | Crizotinib N=142
Adverse Reaction | All Grades (%) | Grade 3 or 4 (%) | All Grades (%) | Grade 3 or 4 (%)
Psychiatric
Mood effects [Mood effects (including affective disorder, affect lability, agitation, anger, anxiety, bipolar I disorder, depressed mood, depression, depressive symptom, euphoric mood, intentional self-injury, irritability, mood altered, mood swings, stress).] | 16 | 2 | 5 | 0
Nervous system
Peripheral neuropathy [Peripheral neuropathy (including dysesthesia, gait disturbance, hypoesthesia, motor dysfunction, muscular weakness, neuralgia, neuropathy peripheral, paresthesia, peripheral motor neuropathy, peripheral sensory neuropathy).] | 34 | 2 | 15 | 0.7
Cognitive effects [Cognitive effects (including events from SOC Nervous system disorders: amnesia, cognitive disorder, disturbance in attention, memory impairment, mental impairment; and also including events from SOC Psychiatric disorders: confusional state, delirium, disorientation).] | 21 | 2 | 6 | 0
Headache | 17 | 0 | 18 | 0.7
Dizziness | 11 | 0 | 14 | 0
Sleep effects [Sleep effects (including insomnia, nightmare, sleep disorder, somnambulism).] | 11 | 1.3 | 10 | 0
Respiratory
Dyspnea | 20 | 2.7 | 16 | 2.1
Cough | 16 | 0 | 18 | 0
Respiratory failure | 2.7 | 2 | 0 | 0
Vascular disorders
Hypertension | 18 | 10 | 2.1 | 0
Ocular
Vision disorder [Vision disorder (including diplopia, photophobia, photopsia, vision blurred, visual acuity reduced, visual impairment, vitreous floaters).] | 18 | 0 | 39 | 0.7
Gastrointestinal
Diarrhea | 21 | 1.3 | 52 | 0.7
Nausea | 15 | 0.7 | 52 | 2.1
Constipation | 17 | 0 | 30 | 0.7
Vomiting | 13 | 0.7 | 39 | 1.4
Musculoskeletal and connective tissue
Arthralgia | 19 | 0.7 | 11 | 0
Myalgia [Myalgia (including musculoskeletal pain, myalgia).] | 15 | 0.7 | 7 | 0
Back pain | 15 | 0.7 | 11 | 0
Pain in extremity | 17 | 0 | 8 | 0
General
Edema [Edema (including edema, edema peripheral, eyelid edema, face edema, generalized edema, localized edema, periorbital edema, peripheral swelling, swelling).] | 56 | 4 | 40 | 1.4
Weight gain | 38 | 17 | 13 | 2.1
Fatigue [Fatigue (including asthenia, fatigue).] | 19 | 1.3 | 32 | 2.8
Pyrexia | 17 | 1.3 | 13 | 1.4
Chest pain | 11 | 1.3 | 14 | 0.7
Infections
Upper respiratory tract infection [Upper respiratory tract infection (including upper respiratory infection).] | 11 | 0.7 | 7.7 | 1.4
Pneumonia | 7.4 | 2 | 8.5 | 3.5
Bronchitis | 6.7 | 2 | 2.1 | 0
Skin
Rash [Rash (including dermatitis acneiform, maculopapular rash, rash).] | 11 | 0 | 8.5 | 0
Abbreviations: NCI CTCAE=National Cancer Institute Common Terminology Criteria for Adverse Events; SOC=System organ class.

Additional clinically significant adverse reactions occurring at an incidence between 1% and 10% were speech effects (6.7%) and psychotic effects (3.4%).

Table 3 Laboratory Abnormalities Worsening from Baseline in ≥20% of Patients in Study B7461006
Laboratory Abnormality | LORBRENA N=149 |  | Crizotinib N=142
Laboratory Abnormality | All Grades (%) | Grade 3 or 4 (%) | All Grades (%) | Grade 3 or 4 (%)
Chemistry
Hypertriglyceridemia [N=149 (LORBRENA).] [N=141 (crizotinib).] | 95 | 22 | 27 | 0
Hypercholesterolemia | 91 | 19 | 12 | 0
Increased creatinine | 81 | 0.7 | 99 | 2.1
Increased GGT | 52 | 6 | 41 | 6
Increased AST | 48 | 2 | 75 | 3.5
Hyperglycemia | 48 | 7 | 27 | 2.1
Increased ALT | 44 | 2.7 | 75 | 4.3
Increased CPK | 39 | 2 | 64 | 5
Hypoalbuminemia | 36 | 0.7 | 61 | 6
Increased lipase | 28 | 7 | 34 | 5
Increased alkaline phosphatase | 23 | 0 | 50 | 0.7
Hyperkalemia | 21 | 1.3 | 27 | 2.1
Increased amylase [N=148 (LORBRENA).] | 20 | 1.4 | 32 | 1.4
Hematology
Anemia | 48 | 2 | 38 | 2.8
Activated PTT [N=138 (LORBRENA).] [N=135 (crizotinib).] | 25 | 0 | 14 | 0
Lymphopenia | 23 | 2.7 | 43 | 6
Thrombocytopenia | 23 | 0 | 7 | 0.7
Abbreviations: ALT=alanine aminotransferase; AST=aspartate aminotransferase; CPK=creatine phosphokinase; GGT=gamma glutamyl transferase; NCI CTCAE=National Cancer Institute Common Terminology Criteria for Adverse Events; PTT=partial thromboplastin time.
N=number of patients who had at least one on-study assessment for the parameter of interest.

Previously Treated ALK-Positive Metastatic NSCLC

The data described below reflect exposure to LORBRENA in 295 patients with ALK-positive or ROS1-positive metastatic NSCLC who received LORBRENA 100 mg orally once daily in Study B7461001, a multi-cohort, non-comparative trial [see Clinical Studies (14)]. The median duration of exposure to LORBRENA was 12.5 months (1 day to 35 months) and 52% received LORBRENA for ≥12 months. Patient characteristics were: median age of 53 years (19 to 85 years), age ≥65 years (18%), female (58%), White (49%), Asian (37%), and ECOG performance status 0 or 1 (96%).

The most frequent (≥20%) adverse reactions were edema, peripheral neuropathy, cognitive effects, dyspnea, fatigue, weight gain, arthralgia, mood effects, and diarrhea. Of the worsening laboratory values occurring in ≥20% of patients, the most frequent were hypercholesterolemia, hypertriglyceridemia, anemia, hyperglycemia, increased AST, hypoalbuminemia, increased ALT, increased lipase, and increased alkaline phosphatase.

Serious adverse reactions occurred in 32% of the 295 patients; the most frequently reported serious adverse reactions were pneumonia (3.4%), dyspnea (2.7%), pyrexia (2%), mental status changes (1.4%), and respiratory failure (1.4%). Fatal adverse reactions occurred in 2.7% of patients and included pneumonia (0.7%), myocardial infarction (0.7%), acute pulmonary edema (0.3%), embolism (0.3%), peripheral artery occlusion (0.3%), and respiratory distress (0.3%). Permanent discontinuation of LORBRENA for adverse reactions occurred in 8% of patients.

The most frequent adverse reactions that led to permanent discontinuation were respiratory failure (1.4%), dyspnea (0.7%), myocardial infarction (0.7%), cognitive effects (0.7%) and mood effects (0.7%). Approximately 48% of patients required dose interruption. The most frequent adverse reactions that led to dose interruptions were edema (7%), hypertriglyceridemia (6%), peripheral neuropathy (5%), cognitive effects (4.4%), increased lipase (3.7%), hypercholesterolemia (3.4%), mood effects (3.1%), dyspnea (2.7%), pneumonia (2.7%), and hypertension (2.0%). Approximately 24% of patients required at least 1 dose reduction for adverse reactions. The most frequent adverse reactions that led to dose reductions were edema (6%), peripheral neuropathy (4.7%), cognitive effects (4.1%), and mood effects (3.1%).

Tables 4 and 5 summarize most frequent adverse reactions and laboratory abnormalities, respectively, in patients treated with LORBRENA in Study B7461001.

Table 4 Adverse Reactions Occurring in ≥10% of Patients in Study B7461001 [Adverse reactions were graded using NCI CTCAE version 4.03.]
Adverse Reaction | LORBRENA (N=295)
Adverse Reaction | All Grades (%) | Grade 3 or 4 (%)
Psychiatric
Mood effects [Mood effects (including affective disorder, affect lability, aggression, agitation, anxiety, depressed mood, depression, euphoric mood, irritability, mania, mood altered, mood swings, personality change, stress, suicidal ideation).] | 23 | 1.7
Nervous system
Peripheral neuropathy [Peripheral neuropathy (including burning sensation, carpal tunnel syndrome, dysesthesia, formication, gait disturbance, hypoesthesia, muscular weakness, neuralgia, neuropathy peripheral, neurotoxicity, paresthesia, peripheral sensory neuropathy, sensory disturbance).] | 47 | 2.7
Cognitive effects [Cognitive effects (including events from SOC Nervous system disorders: amnesia, cognitive disorder, dementia, disturbance in attention, memory impairment, mental impairment; and also including events from SOC Psychiatric disorders: attention deficit/hyperactivity disorder, confusional state, delirium, disorientation, reading disorder).] | 27 | 2
Headache | 18 | 0.7
Dizziness | 16 | 0.7
Speech effects [Speech effects (including aphasia, dysarthria, slow speech, speech disorder)] | 12 | 0.3
Sleep effects [Sleep effects (including abnormal dreams, insomnia, nightmare, sleep disorder, sleep talking, somnambulism)] | 10 | 0
Respiratory
Dyspnea | 27 | 5
Cough | 18 | 0
Ocular
Vision disorder [Vision disorder (including blindness, diplopia, photophobia, photopsia, vision blurred, visual acuity reduced, visual impairment, vitreous floaters).] | 15 | 0.3
Gastrointestinal
Diarrhea | 22 | 0.7
Nausea | 18 | 0.7
Constipation | 15 | 0
Vomiting | 12 | 1
Musculoskeletal and connective tissue
Arthralgia | 23 | 0.7
Myalgia [Myalgia (including musculoskeletal pain, myalgia).] | 17 | 0
Back pain | 13 | 0.7
Pain in extremity | 13 | 0.3
General
Edema [Edema (including edema, edema peripheral, eyelid edema, face edema, generalized edema, localized edema, periorbital edema, peripheral swelling, swelling).] | 57 | 3.1
Fatigue [Fatigue (including asthenia, fatigue).] | 26 | 0.3
Weight gain | 24 | 4.4
Pyrexia | 12 | 0.7
Infections
Upper respiratory tract infection [Upper respiratory infection (including fungal upper respiratory infection, upper respiratory infection, viral upper respiratory infection).] | 12 | 0
Skin
Rash [Rash (including dermatitis acneiform, maculopapular rash, pruritic rash, rash).] | 14 | 0.3
Abbreviations: NCI CTCAE=National Cancer Institute Common Terminology Criteria for Adverse Events; SOC=System organ class.

Additional clinically significant adverse reactions occurring at an incidence between 1% and 10% were psychotic effects (7%).

Table 5 Worsening Laboratory Values Occurring in ≥20% of Patients in Study B7461001 [Grades using NCI CTCAE version 4.03.]
Laboratory Abnormality | LORBRENA
Laboratory Abnormality | All Grades (%) | Grade 3 or 4 (%)
Chemistry
Hypercholesterolemia [N=292.] | 96 | 18
Hypertriglyceridemia | 90 | 18
Hyperglycemia [N=293.] | 52 | 5
Increased AST | 37 | 2.1
Hypoalbuminemia [N=291.] | 33 | 1
Increased ALT | 28 | 2.1
Increased lipase [N=290.] | 24 | 10
Increased alkaline phosphatase | 24 | 1
Increased amylase [N=284.] | 22 | 3.9
Hypophosphatemia | 21 | 4.8
Hyperkalemia | 21 | 1
Hypomagnesemia | 21 | 0
Hematology
Anemia | 52 | 4.8
Thrombocytopenia | 23 | 0.3
Lymphopenia | 22 | 3.4
Abbreviations: ALT=alanine aminotransferase; AST=aspartate aminotransferase; NCI CTCAE=National Cancer Institute Common Terminology Criteria for Adverse Events.
N=number of patients who had at least one on-study assessment for the parameter of interest.

7 DRUG INTERACTIONS

7.1 Effect of Other Drugs on LORBRENA

Strong CYP3A Inducers

LORBRENA is contraindicated in patients taking strong CYP3A inducers [see Contraindication (4)]. Discontinue strong CYP3A inducers for 3 plasma half-lives of the strong CYP3A inducer prior to initiating LORBRENA [see Dosage and Administration (2.3)].

Concomitant use of LORBRENA with a strong CYP3A inducer decreased lorlatinib plasma concentrations [see Clinical Pharmacology (12.3)], which may decrease the efficacy of LORBRENA.

Severe hepatotoxicity occurred in healthy subjects receiving LORBRENA with rifampin, a strong CYP3A inducer. In 12 healthy subjects receiving a single 100 mg dose of LORBRENA with multiple daily doses of rifampin, Grade 3 or 4 increases in ALT or AST occurred in 83% of subjects and Grade 2 increases in ALT or AST occurred in 8%. A possible mechanism for hepatotoxicity is through activation of the pregnane X receptor (PXR) by LORBRENA and rifampin, which are both PXR agonists.

Moderate CYP3A Inducers

Avoid concomitant use of moderate CYP3A inducers with LORBRENA. If concomitant use is unavoidable, increase the LORBRENA dose [see Dosage and Administration (2.4)].

Concomitant use of LORBRENA with a moderate CYP3A inducer decreased lorlatinib plasma concentrations, which may decrease the efficacy of LORBRENA [see Clinical Pharmacology (12.3)].

Strong CYP3A Inhibitors

Avoid concomitant use of LORBRENA with a strong CYP3A inhibitor. If concomitant use cannot be avoided, reduce the LORBRENA dosage [see Dosage and Administration (2.4)].

Concomitant use with a strong CYP3A inhibitor increased lorlatinib plasma concentrations [see Clinical Pharmacology (12.3)], which may increase the incidence and severity of adverse reactions of LORBRENA.

Fluconazole

Avoid concomitant use of LORBRENA with fluconazole. If concomitant use cannot be avoided, reduce the LORBRENA dosage [see Dosage and Administration (2.4)].

Concomitant use of LORBRENA with fluconazole may increase lorlatinib plasma concentrations [see Clinical Pharmacology (12.3)], which may increase the incidence and severity of adverse reactions of LORBRENA.

7.2 Effect of LORBRENA on Other Drugs

Certain CYP3A Substrates

Avoid concomitant use of LORBRENA with certain CYP3A substrates, for which minimal concentration changes may lead to serious therapeutic failures. If concomitant use is unavoidable, increase the CYP3A substrate dosage in accordance with approved product labeling.

LORBRENA is a moderate CYP3A inducer. Concomitant use of LORBRENA decreases the concentration of CYP3A substrates [see Clinical Pharmacology (12.3)], which may reduce the efficacy of these substrates.

Certain P-glycoprotein (P-gp) Substrates

Avoid concomitant use of LORBRENA with certain P-gp substrates for which minimal concentration changes may lead to serious therapeutic failures. If concomitant use is unavoidable, increase the P-gp substrate dosage in accordance with approved product labeling.

LORBRENA is a moderate P-gp inducer. Concomitant use of LORBRENA decreases the concentration of P-gp substrates [see Clinical Pharmacology (12.3)], which may reduce the efficacy of these substrates.

8 USE IN SPECIFIC POPULATIONS

8.1 Pregnancy

Risk Summary

Based on findings from animal studies and its mechanism of action [see Clinical Pharmacology (12.1)], LORBRENA can cause embryo-fetal harm when administered to a pregnant woman. There are no available data on LORBRENA use in pregnant women. Administration of lorlatinib to pregnant rats and rabbits by oral gavage during the period of organogenesis resulted in malformations, increased post-implantation loss, and abortion at maternal exposures that were equal to or less than the human exposure at the recommended dose of 100 mg once daily based on AUC (see Data). Advise a pregnant woman of the potential risk to a fetus.

In the U.S. general population, the estimated background risk of major birth defects and miscarriage in clinically recognized pregnancies are 2 to 4% and 15 to 20%, respectively.

Data

Animal Data

Preliminary embryo-fetal development studies investigating the administration of lorlatinib during the period of organogenesis were conducted in rats and rabbits. In rabbits, lorlatinib administration resulted in abortion and total loss of pregnancy at doses of 15 mg/kg (approximately 3 times the human exposure at the recommended dose of 100 mg) or greater. At a dose of 4 mg/kg (approximately 0.6 times the human exposure at the recommended dose of 100 mg) toxicities included increased post-implantation loss and malformations including rotated limbs, malformed kidneys, domed head, high arched palate, and dilation of the cerebral ventricles. In rats, administration of lorlatinib resulted in total loss of pregnancy at doses of 4 mg/kg (approximately 5 times the human exposure at the recommended dose of 100 mg) or greater. At a dose of 1 mg/kg (approximately equal to the human exposure at the recommended dose of 100 mg) there was increased post-implantation loss, decreased fetal body weight, and malformations including gastroschisis, rotated limbs, supernumerary digits, and vessel abnormalities.

8.2 Lactation

Risk Summary

There are no data on the presence of lorlatinib or its metabolites in either human or animal milk or its effects on the breastfed infant or on milk production. Because of the potential for serious adverse reactions in breastfed infants, instruct women not to breastfeed during treatment with LORBRENA and for 7 days after the final dose.

8.3 Females and Males of Reproductive Potential

Pregnancy Testing

Verify pregnancy status in females of reproductive potential prior to initiating LORBRENA [see Use in Specific Populations (8.1)].

Contraception

LORBRENA can cause embryo-fetal harm when administered to a pregnant woman [see Use in Specific Populations (8.1)].

Females

Advise female patients of reproductive potential to use effective non-hormonal contraception during treatment with LORBRENA and for at least 6 months after the final dose. Advise females of reproductive potential to use a non-hormonal method of contraception, because LORBRENA can render hormonal contraceptives ineffective [see Drug Interactions (7.2)].

Males

Based on genotoxicity findings, advise males with female partners of reproductive potential to use effective contraception during treatment with LORBRENA and for at least 3 months after the final dose [see Nonclinical Toxicology (13.1)].

Infertility

Males

Based on findings from animal studies, LORBRENA may transiently impair male fertility [see Nonclinical Toxicology (13.1)].

8.4 Pediatric Use

The safety and effectiveness of LORBRENA in pediatric patients have not been established.

8.5 Geriatric Use

Of the patients in Study B7461001 (N=295) and Study B7461006 (N=149) who received 100 mg LORBRENA orally once daily, 18% and 40% of patients, respectively, were aged 65 years or older. No clinically important differences in safety or efficacy were observed between patients aged 65 years or older and younger patients.

8.6 Hepatic Impairment

In patients with severe hepatic impairment (Child-Pugh C), the recommended dosage of LORBRENA is 50 mg orally once daily [see Dosage and Administration (2.5) and Clinical Pharmacology (12.3)].

No dose adjustment is recommended for patients with mild (total bilirubin ≤ ULN with AST > ULN or total bilirubin >1 to 1.5 × ULN with any AST) to moderate (Child-Pugh B) hepatic impairment [see Clinical Pharmacology (12.3)].

8.7 Renal Impairment

In patients with CLcr 15 to <30 mL/min (estimated by Cockcroft‑Gault), the recommended dosage of LORBRENA is 75 mg orally once daily [see Dosage and Administration (2.6) and Clinical Pharmacology (12.3)].

No dose adjustment is recommended for patients with CLcr 30 to 89 mL/min (estimated by Cockcroft‑Gault) [see Clinical Pharmacology (12.3)].

11 DESCRIPTION

LORBRENA (lorlatinib) is a kinase inhibitor for oral administration. The molecular formula is C21H19FN6O2 (anhydrous form) and the molecular weight is 406.41 Daltons. The chemical name is (10R)-7-amino-12-fluoro-2,10,16-trimethyl-15-oxo-10,15,16,17-tetrahydro-2H-4,8-methenopyrazolo[4,3-h][2,5,11] benzoxadiazacyclotetradecine-3-carbonitrile. The chemical structure is shown below:

Lorlatinib is a white to off-white powder with a pKa of 4.92. The solubility of lorlatinib in aqueous media decreases over the range pH 2.55 to pH 8.02 from 32.38 mg/mL to 0.17 mg/mL. The log of the distribution coefficient (octanol/water) at pH 9 is 2.45.

LORBRENA is supplied as tablets containing 25 mg or 100 mg of lorlatinib with the following inactive ingredients: microcrystalline cellulose, dibasic calcium phosphate anhydrous, sodium starch glycolate, and magnesium stearate. The film-coating contains hydroxypropyl methylcellulose (HPMC) 2910/hypromellose, lactose monohydrate, macrogol/polyethylene glycol (PEG) 3350, triacetin, titanium dioxide, ferrosoferric oxide/black iron oxide, and iron oxide red.

12 CLINICAL PHARMACOLOGY

12.1 Mechanism of Action

Lorlatinib is a kinase inhibitor with in vitro activity against ALK and ROS1 as well as TYK1, FER, FPS, TRKA, TRKB, TRKC, FAK, FAK2, and ACK. Lorlatinib demonstrated in vitro activity against multiple mutant forms of the ALK enzyme, including some mutations detected in tumors at the time of disease progression on crizotinib and other ALK inhibitors.

In mice subcutaneously implanted with tumors harboring EML4 fusions with either ALK variant 1 or ALK mutations, including the G1202R and I1171T mutations detected in tumors at the time of disease progression on ALK inhibitors, administration of lorlatinib resulted in antitumor activity. Lorlatinib also demonstrated anti-tumor activity and prolonged survival in mice implanted intracranially with EML4-ALK-driven tumor cell lines. The overall antitumor activity of lorlatinib in in vivo models was dose-dependent and correlated with inhibition of ALK phosphorylation.

12.2 Pharmacodynamics

Exposure-response relationships for Grade 3 or 4 hypercholesterolemia and for any Grade 3 or 4 adverse reaction were observed at steady-state exposures achieved at the recommended dosage, with higher probability of the occurrence of adverse reactions with increasing lorlatinib exposure.

Cardiac Electrophysiology

In 295 patients who received LORBRENA at the recommended dosage of 100 mg once daily and had an ECG measurement in Study B7461001, the maximum mean change from baseline for PR interval was 16.4 ms (2-sided 90% upper confidence interval [CI] 19.4 ms). Among the 284 patients with PR interval <200 ms at baseline, 14% had PR interval prolongation ≥200 ms after starting LORBRENA. The prolongation of PR interval occurred in a concentration-dependent manner. Atrioventricular block occurred in 1% of patients.

In 275 patients who received LORBRENA at the recommended dosage in the activity-estimating portion of Study B7461001, no large mean increases from baseline in the QTcF interval (i.e., >20 ms) were detected.

12.3 Pharmacokinetics

At the recommended dosage, the mean (coefficient of variation [CV] %) maximum plasma concentration (Cmax) is 577 ng/mL (42%) and the AUC0-24h is 5,650 ng·h/mL (39%). Steady-state lorlatinib Cmax increases proportionally and AUC increased slightly less than proportionally over the dose range of 10 mg to 200 mg orally once daily (0.1 to 2 times the recommended dosage).

Absorption

The median lorlatinib Tmax is 1.2 hours (0.5 to 4 hours) following a single oral 100 mg dose and 2 hours (0.5 to 23 hours) following 100 mg orally once daily at steady‑state.

The mean absolute bioavailability is 81% (90% CI 76%, 86%).

Effect of Food

No clinically significant differences in lorlatinib pharmacokinetics were observed following administration of a high fat, high calorie meal (approximately 1000 calories with 150 calories from protein, 250 calories from carbohydrate, and 500 to 600 calories from fat).

Distribution

Lorlatinib is 66% bound to plasma proteins, in vitro. The blood-to-plasma ratio is 0.99, in vitro.

Elimination

The mean plasma half‑life (t½) of lorlatinib was 24 hours (40%) after a single oral 100 mg dose of LORBRENA. The mean oral clearance (CL/F) was 11 L/h (35%) following a single oral 100 mg dose and increased to 18 L/h (39%) at steady‑state, suggesting autoinduction.

Metabolism

Lorlatinib is metabolized primarily by CYP3A4 and UGT1A4, with minor contribution from CYP2C8, CYP2C19, CYP3A5, and UGT1A3.

In plasma, a benzoic acid metabolite (M8) of lorlatinib resulting from the oxidative cleavage of the amide and aromatic ether bonds of lorlatinib accounted for 21% of the circulating radioactivity. The oxidative cleavage metabolite, M8, is pharmacologically inactive.

Excretion

Following a single oral 100 mg dose of radiolabeled lorlatinib, 48% of the radioactivity was recovered in urine (<1% as unchanged) and 41% in feces (about 9% as unchanged).

Specific Populations

No clinically significant differences in lorlatinib pharmacokinetics were observed based on age (19 to 85 years), sex, race/ethnicity (52% White, 8% Black, 27% Asian), body weight (32-156 kg), CLcr 30 to 89 mL/min (estimated by Cockcroft Gault), mild (total bilirubin ≤ ULN and AST > ULN or total bilirubin > 1 to 1.5 × ULN and any AST) to moderate (Child-Pugh B) hepatic impairment, or metabolizer phenotypes for CYP3A5 and CYP2C19.

Patients with Moderate or Severe Hepatic Impairment

Following administration of a single oral 100 mg dose of LORBRENA, lorlatinib AUC increased 1.1-fold in non-cancer subjects with moderate hepatic impairment (Child-Pugh B) and 1.8-fold in non-cancer subjects with severe hepatic impairment (Child-Pugh C).

Patients with Renal Impairment

Following administration of a single oral 100 mg dose of LORBRENA, lorlatinib AUC increased 1.4-fold in subjects with CLcr 15 to <30 mL/min (estimated by Cockcroft Gault). The pharmacokinetics of lorlatinib have not been studied in patients with end-stage renal disease requiring hemodialysis.

Drug Interaction Studies

Clinical Studies and Model-Informed Approaches

Strong CYP3A Inducers: Rifampin (a strong CYP3A inducer that also activates PXR) 600 mg once daily for 8 days (Days 1 to 8) coadministered with a single oral 100 mg dose of LORBRENA on Day 8 reduced the mean lorlatinib AUC by 85% and Cmax by 76%. Grade 2 to 4 increases in ALT or AST occurred within 3 days. Grade 4 ALT or AST elevations occurred in 50%, Grade 3 ALT or AST elevations in 33%, and Grade 2 ALT or AST elevations occurred in 8% of subjects. ALT and AST returned to within normal limits within 7 to 34 days (median 15 days).

Moderate CYP3A Inducers: Modafinil (a moderate CYP3A inducer) decreased lorlatinib AUC by 23% and Cmax by 22% of a single oral 100 mg dose of LORBRENA.

Strong CYP3A Inhibitors: Itraconazole (a strong CYP3A inhibitor) increased lorlatinib AUC 1.4-fold and Cmax 1.2-fold of a single oral 100 mg dose of LORBRENA.

Fluconazole: Fluconazole is predicted to increase lorlatinib AUC 1.6-fold and Cmax 1.3-fold following concomitant oral administration of 100 mg of LORBRENA once daily and 200 mg fluconazole once daily.

Moderate CYP3A Inhibitors: No clinically significant effect on lorlatinib pharmacokinetics is predicted when used concomitantly with verapamil or erythromycin.

CYP3A Substrates: LORBRENA 150 mg orally once daily for 15 days decreased AUC by 64% and Cmax by 50% of a single oral 2 mg dose of midazolam (a sensitive CYP3A substrate).

CYP2B6 Substrates: LORBRENA 100 mg orally once daily for 15 days decreased AUC by 25% and Cmax by 27% of a single oral 100 mg dose of bupropion (a sensitive CYP2B6 substrate).

CYP2C9 Substrates: LORBRENA 100 mg orally once daily for 15 days decreased AUC by 43% and Cmax by 15% of a single oral 100 mg dose of tolbutamide (a sensitive CYP2C9 substrate).

UGT1A Substrates: LORBRENA 100 mg orally once daily for 15 days decreased AUC by 45% and Cmax by 28% of a single oral 100 mg dose of acetaminophen (a UGT1A substrate).

P-gp Substrates: LORBRENA 100 mg orally once daily for 15 days decreased AUC by 67% and Cmax by 63% of a single oral 60 mg dose of fexofenadine (a P-gp substrate).

Acid-Reducing Agents: Concomitant use of a proton pump inhibitor, rabeprazole, did not have a clinically significant effect on lorlatinib pharmacokinetics.

In Vitro Studies

CYP Enzymes: Lorlatinib is a time-dependent inhibitor as well as an inducer of CYP3A and activates PXR, with the net effect in vivo being induction. Lorlatinib induces CYP2B6 and activates the human constitutive androstane receptor (CAR). Lorlatinib and the major circulating metabolite, M8, do not inhibit CYP1A2, CYP2B6, CYP2C8, CYP2C9, CYP2C19, or CYP2D6. M8 does not inhibit CYP3A.

M8 does not induce CYP1A2, CYP2B6, or CYP3A.

UDP-glucuronosyltransferase (UGT): Lorlatinib and M8 do not inhibit UGT1A1, UGT1A4, UGT1A6, UGT1A9, UGT2B7, or UGT2B15.

Transporter Systems: Lorlatinib is an inhibitor of P-gp and activates PXR (potential to induce P-gp), with the net effect in vivo being induction.

Lorlatinib inhibits OCT1, OAT3, MATE1, and intestinal BCRP. Lorlatinib does not inhibit OATP1B1, OATP1B3, OAT1, OCT2, MATE2K, or systemic BCRP. M8 does not inhibit P‑gp, BCRP, OATP1B1, OATP1B3, OAT1, OAT3, OCT1, OCT2, MATE1, or MATE2K.

13 NONCLINICAL TOXICOLOGY

13.1 Carcinogenesis, Mutagenesis, Impairment of Fertility

Carcinogenicity studies have not been conducted with lorlatinib. Lorlatinib was aneugenic in an in vitro assay in human lymphoblastoid TK6 cells and positive for micronuclei formation in vivo in the bone marrow of rats. Lorlatinib was not mutagenic in an in vitro bacterial reverse mutation (Ames) assay.

Dedicated fertility studies were not conducted with lorlatinib. Findings in male reproductive organs occurred in repeat-dose toxicity studies and included lower testicular, epididymal, and prostate weights; testicular tubular degeneration/atrophy; prostatic atrophy; and/or epididymal inflammation at 15 mg/kg/day and 7 mg/kg/day in rats and dogs, respectively (approximately 8 and 2 times, respectively, the human exposure at the recommended dose of 100 mg based on AUC). The effects on male reproductive organs were reversible.

13.2 Animal Toxicology and/or Pharmacology

Distended abdomen, skin rash, and increased cholesterol and triglycerides occurred in animals. These findings were accompanied by hyperplasia and dilation of the bile ducts in the liver and acinar atrophy of the pancreas in rats at 15 mg/kg/day and in dogs at 2 mg/kg/day (approximately 8 and 0.5 times, respectively, the human exposure at the recommended dose of 100 mg based on AUC). All effects were reversible within the recovery period.

14 CLINICAL STUDIES

Previously Untreated ALK-Positive Metastatic NSCLC (CROWN Study)

The efficacy of LORBRENA for the treatment of patients with ALK-positive NSCLC who had not received prior systemic therapy for metastatic disease was established in an open-label, randomized, active-controlled, multicenter study (Study B7461006; NCT03052608). Patients were required to have an ECOG performance status of 0–2 and ALK-positive NSCLC as identified by the VENTANA ALK (D5F3) CDx assay. Neurologically stable patients with treated or untreated asymptomatic CNS metastases, including leptomeningeal metastases, were eligible. Patients were required to have finished radiation therapy, at least 2 weeks (for stereotactic or partial radiation) or 4 weeks (for whole brain irradiation) prior to randomization. Patients with severe acute or chronic psychiatric conditions, including recent (within the past year) or active suicidal ideation or behavior, were excluded.

Patients were randomized 1:1 to receive LORBRENA 100 mg orally once daily or crizotinib 250 mg orally twice daily. Randomization was stratified by ethnic origin (Asian vs. non-Asian) and the presence or absence of CNS metastases at baseline. Treatment on both arms was continued until disease progression or unacceptable toxicity. The major efficacy outcome measure was progression-free survival (PFS) as determined by Blinded Independent Central Review (BICR) according to Response Evaluation Criteria in Solid Tumors (RECIST) version 1.1 (v1.1). Additional efficacy outcome measures were overall survival (OS) and tumor assessment related data by BICR, including overall response rate (ORR), and duration of response (DOR). In patients with measurable CNS metastases at baseline, additional outcome measures were intracranial overall response rate (IC-ORR) and intracranial duration of response (IC-DOR) by BICR.

A total of 296 patients were randomized to LORBRENA (n=149) or crizotinib (n=147). The demographic characteristics of the overall study population were: median age 59 years (range: 26 to 90 years), age ≥65 years (35%), 59% female, 49% White, 44% Asian, and 0.3% Black. The ECOG performance status at baseline was 0 or 1 in 96% of patients. The majority of patients had adenocarcinoma (95%) and never smoked (59%). CNS metastases were present in 26% (n=78) of patients: of these, 30 patients had measurable CNS lesions.

Efficacy results from Study B7461006 as assessed by BICR are summarized in Table 6 and Figure 1. Results demonstrated a significant improvement in PFS for the LORBRENA arm over the crizotinib arm. At the data cutoff point OS data was not mature.

Table 6 Efficacy Results in Study B7461006 (CROWN)
Efficacy Parameter | LORBRENA N=149 | Crizotinib N=147
Progression-free survival
Number of events, n (%) | 41 (28%) | 86 (59%)
Progressive disease, n (%) | 32 (22%) | 82 (56%)
Death, n (%) | 9 (6%) | 4 (3%)
Median, months (95% CI) [Based on the Brookmeyer and Crowley method.] | NE (NE, NE) | 9.3 (7.6, 11.1)
Hazard ratio (95% CI) [Hazard ratio based on Cox proportional hazards model.] | 0.28 (0.19, 0.41)
p-value [p-value based on 1-sided stratified log-rank test.] | <0.0001
Overall response rate
Overall response rate (95% CI) [Using exact method based on binomial distribution.] | 76% (68, 83) | 58% (49, 66)
Complete response | 3% | 0%
Partial response | 73% | 58%
Duration of response
Number of responders, n | 113 | 85
Median, months (Range) | NE (0.9, 31.3) | 11 (1.1, 27.5)
Response duration ≥6 months, n (%) | 101 (89%) | 53 (62%)
Response duration ≥12 months, n (%) | 79 (70%) | 23 (27%)
Response duration ≥18 months, n (%) | 34 (30%) | 9 (11%)
Abbreviations: CI=confidence interval; N=number of patients; NE=not estimable; PFS=progression‑free survival.

Figure 1: Kaplan-Meier Plot of Progression-Free Survival by BICR in Study B7461006 (CROWN)

The results of prespecified exploratory analyses of intracranial response rate in 30 patients with measurable CNS lesions at baseline as assessed by BICR are summarized in Table 7.

Table 7 Intracranial Response Rate in Patients with Measurable Intracranial Lesions in CROWN
Intracranial Tumor Response Assessment | LORBRENA N=17 | Crizotinib N=13
Intracranial response rate (95% CI) [Using exact method based on binomial distribution.] | 82% (57, 96) | 23% (5, 54)
Complete response | 71% | 8%
Duration of response
Number of responders, n | 14 | 3
Response duration ≥12 months, n (%) | 11 (79%) | 0
Abbreviations: CI=confidence interval; N/n=number of patients.

ALK-Positive Metastatic NSCLC Previously Treated with an ALK Kinase Inhibitor

The efficacy of LORBRENA was demonstrated in a subgroup of patients with ALK-positive metastatic NSCLC previously treated with one or more ALK kinase inhibitors who were enrolled in a non-randomized, dose-ranging and activity-estimating, multi-cohort, multicenter study (Study B7461001; NCT01970865). Patients included in this subgroup were required to have metastatic disease with at least 1 measurable target lesion according to RECIST v1.1, ECOG performance status of 0 to 2, and documented ALK rearrangement in tumor tissue as determined by fluorescence in situ hybridization (FISH) assay or by Immunohistochemistry (IHC), and received LORBRENA 100 mg orally once daily. Patients with asymptomatic CNS metastases, including patients with stable or decreasing steroid use within 2 weeks prior to study entry, were eligible. Patients with severe, acute, or chronic psychiatric conditions including suicidal ideation or behavior were excluded. In addition, for patients with ALK-positive metastatic NSCLC, the extent and type of prior treatment was specified for each individual cohort (see Table 8). The major efficacy outcome measures were ORR and intracranial ORR, according to RECIST v1.1, as assessed by Independent Central Review (ICR) committee. Data were pooled across all subgroups listed in Table 8. Additional efficacy outcome measures included DOR, and intracranial DOR.

A total of 215 patients were enrolled across the subgroups in Table 8. The distribution of patients by type and extent of prior therapy is provided in Table 8. The demographic characteristics across all 215 patients were: 59% female, 51% White, 34% Asian, and the median age was 53 years (29 to 85 years) with 18% of patients ≥65 years. The ECOG performance status at baseline was 0 or 1 in 96% of patients. All patients had metastatic disease and 95% had adenocarcinoma. Brain metastases as identified by ICR were present in 69% of patients; of these, 60% had received prior radiation to the brain and 60% (n=89) had measurable disease per ICR.

Table 8 Extent of Prior Therapy in the Subgroup of Patients with Previously Treated ALK-Positive Metastatic NSCLC in Study B7461001
Extent of prior therapy | Number of patients
Prior crizotinib and no prior chemotherapy [Chemotherapy administered in the metastatic setting.] | 29
Prior crizotinib and 1–2 lines of prior chemotherapy | 35
Prior ALK inhibitor (not crizotinib) with or without prior chemotherapy | 28
Two prior ALK inhibitors with or without prior chemotherapy | 75
Three prior ALK inhibitors with or without prior chemotherapy | 48
Total | 215
Abbreviations: ALK=anaplastic lymphoma kinase; NSCLC=non-small cell lung cancer.

Efficacy results for Study B7461001 are summarized in Tables 9 and 10.

Table 9 Efficacy Results in Study B7461001
Efficacy Parameter | Overall N=215
Overall response rate [Per Independent Central Review.] (95% CI) [Using exact method based on binomial distribution.] | 48% (42, 55)
Complete response | 4%
Partial response | 44%
Duration of response
Median, months [Estimated using the Kaplan-Meier method.] (95% CI) | 12.5 (8.4, 23.7)
Abbreviations: CI=confidence interval; N=number of patients.

An assessment of intracranial ORR and the duration of response for CNS metastases in the subgroup of 89 patients in Study B7461001 with baseline measurable lesions in the CNS according to RECIST v1.1 are summarized in Table 10. Of these, 56 (63%) patients received prior brain radiation, including 42 patients (47%) who completed brain radiation treatment at least 6 months before starting treatment with LORBRENA.

Table 10 Intracranial Response Rate in Patients with Measurable Intracranial Lesions in Study B7461001
Efficacy Parameter | Intracranial N=89
Intracranial response rate [Per Independent Central Review.] (95% CI) [Using exact method based on binomial distribution.] | 60% (49, 70)
Complete response | 21%
Partial response | 38%
Duration of response
Median, months [Estimated using the Kaplan-Meier method.] (95% CI) | 19.5 (12.4, NR)
Abbreviations: CI=confidence interval; N=number of patients; NR=not reached.

In exploratory analyses conducted in subgroups defined by prior therapy, the response rates to LORBRENA were:

- ORR = 39% (95% CI: 30, 48) in 119 patients who received crizotinib and at least one other ALK inhibitor, with or without prior chemotherapy
- ORR = 31% (95% CI: 9, 61) in 13 patients who received alectinib as their only ALK inhibitor, with or without prior chemotherapy
- ORR = 46% (95% CI: 19, 75) in 13 patients who received ceritinib as their only ALK inhibitor, with or without prior chemotherapy

16 HOW SUPPLIED/STORAGE AND HANDLING

Table 11 describes the available strengths and package configurations for LORBRENA:

Table 11 LORBRENA Tablets
Strength (mg) | Package Configuration | NDC | Description
25 | 30 tablets bottle with a child-resistant closure | 0069-0227-01 | 8 mm round, tan, immediate release film‑coated tablet, debossed with “Pfizer” on one side and “25” and “LLN” on the other side
25 | 120 tablets bottle with a child-resistant closure | 0069-0227-03 | 8 mm round, tan, immediate release film‑coated tablet, debossed with “Pfizer” on one side and “25” and “LLN” on the other side
100 | 30 tablets bottle with a child-resistant closure | 0069-0231-01 | 8.5 mm × 17 mm oval, lavender, immediate release, film‑coated tablet, debossed with “Pfizer” on one side and “LLN 100” on the other side

STORAGE AND HANDLING

Store at 20°C to 25°C (68°F to 77°F); excursions permitted between 15°C to 30°C (59°F to 86°F) [see USP Controlled Room Temperature].

17 PATIENT COUNSELING INFORMATION

Advise the patient to read the FDA-approved patient labeling (Patient Information).

Risk of Serious Hepatotoxicity with Concomitant Use of Strong CYP3A Inducers

Inform patients of the potential risk of hepatotoxicity with the concomitant use of strong CYP3A inducers.

Advise patients to inform their healthcare providers of all medications they are taking, including prescription medicines, over-the-counter drugs, vitamins, and herbal products (e.g., St. John's wort) [see Warnings and Precautions (5.1)].

Central Nervous System (CNS) Effects

Advise patients to notify their healthcare provider if they experience new or worsening CNS symptoms [see Warnings and Precautions (5.2)].

Hyperlipidemia

Inform patients that serum cholesterol and triglycerides will be monitored during treatment. Advise patients that initiation or an increase in the dose of lipid-lowering agents may be required [see Warnings and Precautions (5.3)].

Atrioventricular (AV) Block

Inform patients of the risks of AV block. Advise patients to contact their healthcare provider immediately to report new or worsening cardiac symptoms [see Warnings and Precautions (5.4)].

Interstitial Lung Disease (ILD)/Pneumonitis

Inform patients of the risks of severe ILD/pneumonitis. Advise patients to contact their healthcare provider immediately to report new or worsening respiratory symptoms [see Warnings and Precautions (5.5)].

Hypertension

Advise patients of the risks of hypertension and to promptly report signs or symptoms of hypertension to their healthcare provider. Advise patients with hypertension that antihypertension medications may need to be initiated or adjusted during treatment with LORBRENA [see Warnings and Precautions (5.6)].

Hyperglycemia

Inform patients of the risks of new or worsening hyperglycemia and of the need to periodically monitor glucose levels and to promptly report hyperglycemia to their healthcare provider. Advise patients with newly occurring hyperglycemia during treatment with LORBRENA that antihyperglycemic medications may need to be initiated. Inform patients with diabetes mellitus or glucose intolerance that antihyperglycemic medications may need to be adjusted during treatment with LORBRENA [see Warnings and Precautions (5.7)].

Embryo-Fetal Toxicity

Advise females of reproductive potential of the potential risk to a fetus. Advise females to inform their healthcare provider of a known or suspected pregnancy [see Warnings and Precautions (5.8), Use in Specific Populations (8.1)].

Advise females of reproductive potential to use effective non-hormonal contraception during treatment with LORBRENA and for at least 6 months after the final dose [see Use in Specific Populations (8.3)].

Advise male patients with female partners of reproductive potential to use effective contraception during treatment with LORBRENA and for at least 3 months after the final dose [see Use in Specific Populations (8.3), Nonclinical Toxicology (13.1)].

Lactation

Advise women not to breastfeed during treatment with LORBRENA and for 7 days after the final dose [see Use in Specific Populations (8.2)].

Infertility

Advise males of reproductive potential that LORBRENA may transiently impair fertility [see Use in Specific Populations (8.3), Nonclinical Toxicology (13.1)].

This product's labeling may have been updated. For the most recent prescribing information, please visit www.Pfizer.com.

LAB-1162-8.0

PATIENT INFORMATION
LORBRENA (lor-BREN-ah)
(lorlatinib)
tablets

What is the most important information I should know about LORBRENA?

LORBRENA can cause serious side effects, including:

- Liver problems due to interactions with other medicines. Liver problems can be severe. It is important to know what medicines not to take during treatment with LORBRENA. See “Tell your healthcare provider about all the medicines you take, including.”
- Central nervous system (CNS) effects. CNS effects can be severe. Tell your healthcare provider if you get any new or worsening symptoms of CNS effects, including:
  - problems with thinking, such as forgetfulness or confusion
  - changes in mood, such as depression and thoughts about suicide or dying
  - psychotic effects, such as seeing or hearing things that are not real (hallucinations)
  - seizures
  - changes in speech
  - changes in sleep
- Increases in the cholesterol and triglycerides (lipid) levels in your blood. Most people will get an increase in the lipid levels in their blood during treatment with LORBRENA.
  - If you get increases in the lipid levels in your blood, your healthcare provider may start you on a new medicine or increase your dose if you are already taking a medicine to lower the lipid levels in your blood.
  - Your healthcare provider will do blood tests to check the lipid levels in your blood before starting treatment, 1 and 2 months after starting treatment, and during treatment with LORBRENA.
- Heart problems. LORBRENA can cause very slow or abnormal heartbeats. Your healthcare provider will check your heart rhythm (electrocardiogram or EKG) before starting and during treatment with LORBRENA. In some people, these problems are severe, and you may need to get a pacemaker. Tell your healthcare provider right away if you feel dizzy or faint or have abnormal heartbeats.
- Lung problems. LORBRENA can cause severe or life-threatening swelling (inflammation) of the lungs during treatment that can lead to death. Symptoms may be like those from lung cancer. Tell your healthcare provider right away if you get any new or worsening symptoms of lung problems, including trouble breathing, shortness of breath, cough, or fever.
- High blood pressure (hypertension). Your healthcare provider will check your blood pressure before starting treatment, 2 weeks after starting treatment, and then at least every month during treatment with LORBRENA. Your healthcare provider may start or change your blood pressure medicine if you get high blood pressure. Tell your healthcare provider right away if you get signs or symptoms of high blood pressure, including: headaches, dizziness, blurred vision, chest pain or shortness of breath.
- High blood sugar (hyperglycemia). LORBRENA can cause new or worsening increases in your blood sugar levels. Your healthcare provider will do blood tests to check your blood sugar levels before starting and during treatment with LORBRENA. Your healthcare provider may start or change your blood sugar medicine if you get high blood sugar. Tell your healthcare provider right away if you get any signs and symptoms of high blood sugar, including:

- feeling very thirsty
- needing to urinate more than usual
- feeling very hungry

- feeling sick to your stomach
- feeling weak or tired
- feeling confused

If you get serious side effects during treatment, your healthcare provider may change your dose, temporarily stop, or permanently stop treatment with LORBRENA.
See "What are possible side effects of LORBRENA?" for more information about side effects.

What is LORBRENA?

LORBRENA is a prescription medicine used to treat adults with non-small cell lung cancer (NSCLC):

- that is caused by an abnormal anaplastic lymphoma kinase (ALK) gene, and
- that has spread to other parts of your body (metastatic).

Your healthcare provider will perform a test to make sure that LORBRENA is right for you.
It is not known if LORBRENA is safe and effective in children.

Do not take LORBRENA if you take certain other medicines called strong CYP3A inducers. Ask your healthcare provider for a list of these medicines if you are not sure.

Before taking LORBRENA, tell your healthcare provider about all of your medical conditions, including if you:

- have kidney problems
- have liver problems
- have had episodes of depression or seizures
- have high levels of cholesterol or triglycerides in your blood
- have problems with your heart beat
- have lung or breathing problems
- have high blood pressure
- have diabetes or high blood sugar
- are pregnant or plan to become pregnant. LORBRENA can harm your unborn baby.
Females who are able to become pregnant:
  1. Your healthcare provider will do a pregnancy test before you start treatment with LORBRENA.
  2. Tell your healthcare provider right away if you become pregnant or think you may be pregnant during treatment with LORBRENA.
  3. Use effective non-hormonal birth control during treatment and for at least 6 months after the final dose of LORBRENA.
  4. Birth control pills (oral contraceptives) and other hormonal forms of birth control may not be effective if used during treatment with LORBRENA. Talk to your healthcare provider about birth control choices that are right for you during this time.
Males with female partners who are able to become pregnant:
  1. Use effective birth control during treatment and for at least 3 months after the final dose of LORBRENA.
- are breastfeeding or plan to breastfeed. It is not known if LORBRENA passes into your breast milk. Do not breastfeed during treatment and for 7 days after the final dose of LORBRENA. Talk to your healthcare provider about the best way to feed your baby during this time.

Tell your healthcare provider about all the medicines you take, including prescription medicines, over-the-counter medicines, vitamins, and herbal supplements. Taking LORBRENA with certain other medicines may increase your risk of side effects and may affect the way LORBRENA or the other medicines work.
Know the medicines you take. Keep a list of them to show to your healthcare provider and pharmacist when you get a new medicine.

How should I take LORBRENA?

- Take LORBRENA exactly as your healthcare provider tells you to take it. Do not change your dose or stop taking LORBRENA unless your healthcare provider tells you to.
- Swallow LORBRENA tablets whole. Do not chew, crush, or split LORBRENA tablets. Do not take LORBRENA tablets if they are broken, cracked, or not intact.
- Take LORBRENA 1 time a day, at the same time each day.
- You may take LORBRENA with or without food.
- If you miss a dose, take it as soon as you remember. However, if it is within 4 hours of the time to take your next dose, just take your next dose at your regular time. Do not take 2 doses of LORBRENA at the same time to make up for the missed dose.
- If you vomit after taking a dose of LORBRENA, do not take an extra dose. Take your next dose at your regular time.

What are the possible side effects of LORBRENA?

- See "What is the most important information I should know about LORBRENA?"

The most common side effects of LORBRENA include:

- swelling in your arms, legs, hands and feet (edema)
- numbness and tingling feeling in your joints or arms and legs (peripheral neuropathy)
- weight gain
- problems with thinking, such as forgetfulness or confusion
- tiredness (fatigue)

- difficulty breathing
- pain in your joints
- diarrhea
- changes in mood, such as depression and irritability
- increased cholesterol and triglyceride levels in the blood
- cough

LORBRENA may cause decreased fertility in males, which may affect your ability to have children. Talk to your healthcare provider if you have concerns about fertility.

These are not all of the possible side effects of LORBRENA.

Call your doctor for medical advice about side effects. You may report side effects to FDA at 1‑800‑FDA‑1088.

How should I store LORBRENA?

- Store LORBRENA at room temperature between 68°F to 77°F (20°C to 25°C).
- LORBRENA comes in a bottle that contains a child resistant cap.

Keep LORBRENA and all medicines out of the reach of children.

General information about the safe and effective use of LORBRENA.

Medicines are sometimes prescribed for purposes other than those listed in a Patient Information leaflet. Do not use LORBRENA for a condition for which it was not prescribed. Do not give LORBRENA to other people, even if they have the same symptoms that you have. It may harm them. You can ask your pharmacist or healthcare provider for more information about LORBRENA that is written for health professionals.

What are the ingredients in LORBRENA?

Active ingredient: lorlatinib

Inactive ingredients: microcrystalline cellulose, dibasic calcium phosphate anhydrous, sodium starch glycolate, and magnesium stearate.

Film-coating contains: hydroxypropyl methylcellulose (HPMC) 2910/hypromellose, lactose monohydrate, macrogol/polyethylene glycol (PEG) 3350, triacetin, titanium dioxide, ferrosoferric oxide/black iron oxide, and iron oxide red.

For more information, go to www.Pfizer.com.

LAB-1163-6.0

This Patient Information has been approved by the U.S. Food and Drug Administration. Revised: January 2026

PRINCIPAL DISPLAY PANEL - 25 mg Tablet Bottle Label Sample

PROFESSIONAL SAMPLE – NOT FOR SALE

Pfizer
NDC 63539-927-01

Lorbrena®
(lorlatinib) tablets
25 mg

30 Tablets
Rx only